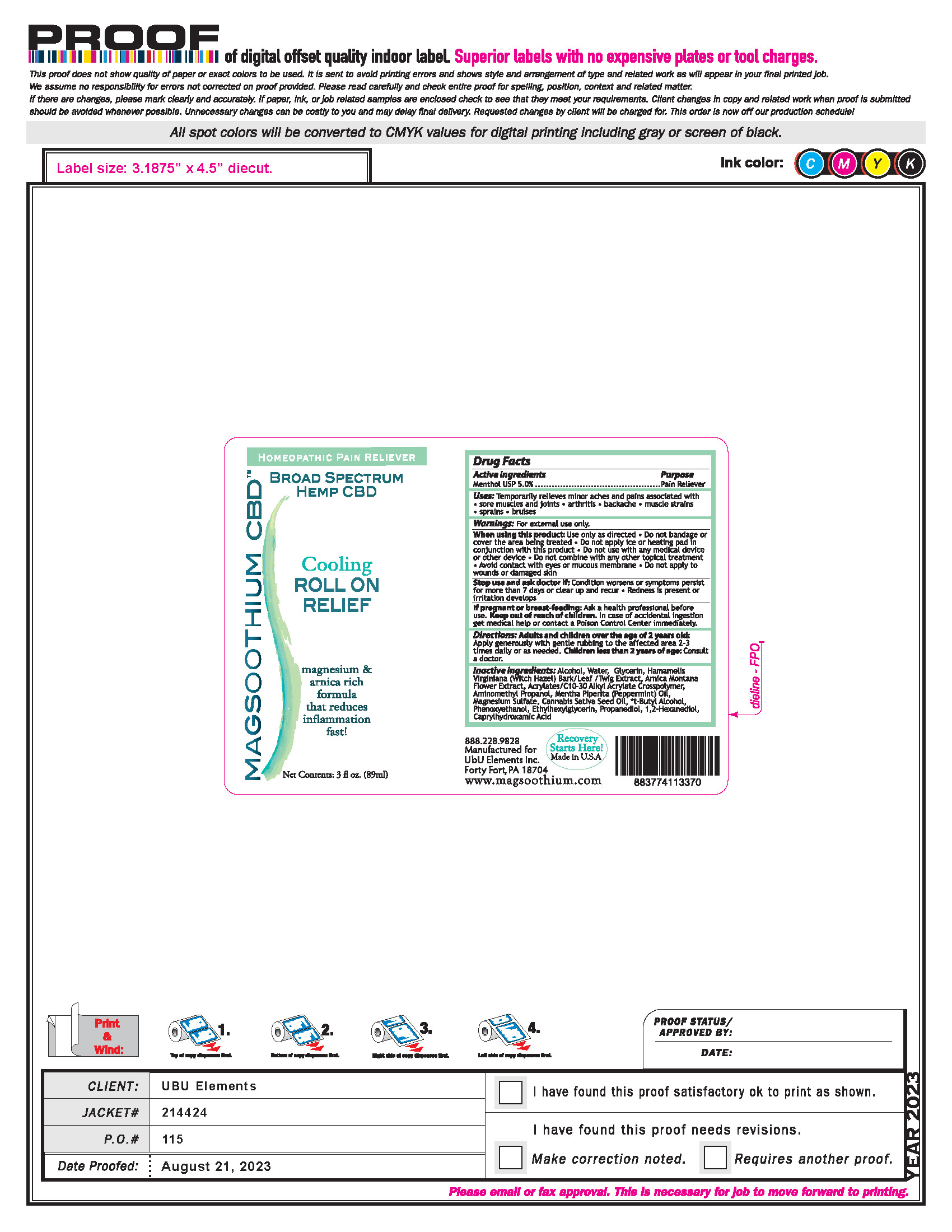 DRUG LABEL: Magsoothium CBD Cooling Roll on Relief
NDC: 83262-005 | Form: LIQUID
Manufacturer: Ubu/Elements, Inc.
Category: otc | Type: HUMAN OTC DRUG LABEL
Date: 20250130

ACTIVE INGREDIENTS: MENTHOL 5 g/100 mL
INACTIVE INGREDIENTS: PHENOXYETHANOL; AMINOMETHYL PROPANOL; ACRYLATES/C10-30 ALKYL ACRYLATE CROSSPOLYMER (60000 MPA.S); ARNICA MONTANA FLOWER; WATER; WITCH HAZEL; T-BUTYL ALCOHOL; ETHYLHEXYLGLYCERIN; ALCOHOL; MENTHA PIPERITA (PEPPERMINT) OIL; CANNABIS SATIVA SEED OIL; CAPRYLHYDROXAMIC ACID; PROPANEDIOL; 1,2-HEXANEDIOL; GLYCERIN; MAGNESIUM SULFATE

Magsoothium CBD Cooling Roll on Relief

Active Ingredients Purpose

Menthol USP 5.0% Pain reliever

PURPOSE

Uses: Temporarily relieves minor aches and pains associated with

- sore musclesand joins
- arthritis
- backache
- muscle strains
- sprains
- bruises

Keep out of reach of children. In case of accidental ingestion get medical help or contact a Poison Control Center immediately.

Stop use and ask a doctor if: Condition worsens or symptoms persist for more than 7 days or clear up and recur

- redness is present or irritation develops

Warnings: For external use only

When using this product: use only as directed

- Do not bandage or cover the are being treated
- Do not apply ice or heating pad in conjunction with this product
- Do not use with any medical device or other device
- Do not combine with any other topical treatment
- Avoid contact with eyes or mucouys membrane
- Do not apply to wounds or damaged skin

DOSAGE AND ADMINISTRATION

Directions: Adults and children over the age of 2 years old: Apply generously with gentle rubbing to the affected area 2-3 times daily or as needed.

Children less than 2 years of age: Consult a doctor

INACTIVE INGREDIENT

Inactive ingredients: Alcohol, Water, Glycerin, Hamamelis Virginiana (Witch Hazel) Bark/Leaf/Twig Extract, Arnica Montana Flower Extract, Acrylates/ C10-30 Alkyl Acrylate Crosspolymer, Aminomethyl Propanol, Mentha Piperita (Peppermint) Oil, Magnesium Sulfate, Cannabis Sativa Seed Oil, t-Butyl Alcohol, Phenoxyethanol, Ethylhexylglycerin, Propanediol, 1,2-Hexanediol, Caprylhydroxamic Acid

PACKAGE LABEL

Broad Spectrum Hemp CBD

Cooling Roll On Relief

Net Contents: 3 fl. oz. (89ml)